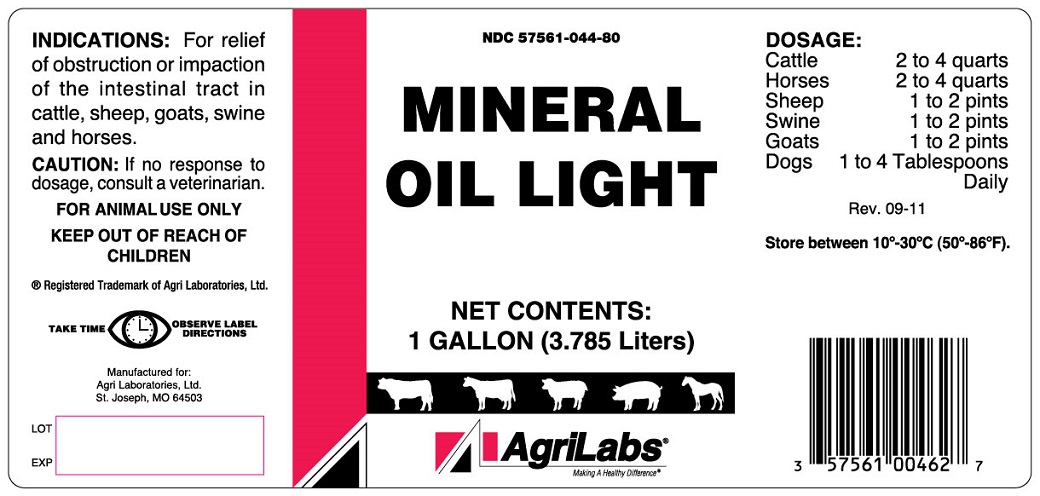 DRUG LABEL: Mineral Oil
NDC: 57561-044 | Form: OIL
Manufacturer: Agri Laboratories Ltd 
Category: animal | Type: OTC ANIMAL DRUG LABEL
Date: 20140810

ACTIVE INGREDIENTS: Light Mineral Oil 3.785 L/3.785 L

MINERAL OIL LIGHT

INDICATIONS AND USAGE

FOR ANIMAL USE ONLY

KEEP OUT OF REACH OF CHILDREN

INDICATIONS

For relief of obstruction or impaction of the intestinal tract in cattle, sheep, goats, swine and horses.

CAUTION

If no response to dosage, consult a veterinarian.

TAKE TIME OBSERVE LABEL DIRECTIONS

DOSAGE

Cattle 2 to 4 quarts
Horses 2 to 4 quarts
Sheep 1 to 2 pints
Swine 1 to 2 pints
Goats 1 to 2 pints
Dogs 1 to 4 tablespoons
Daily

STORAGE AND HANDLING

Store between 10o-30oC (50o-86oF).